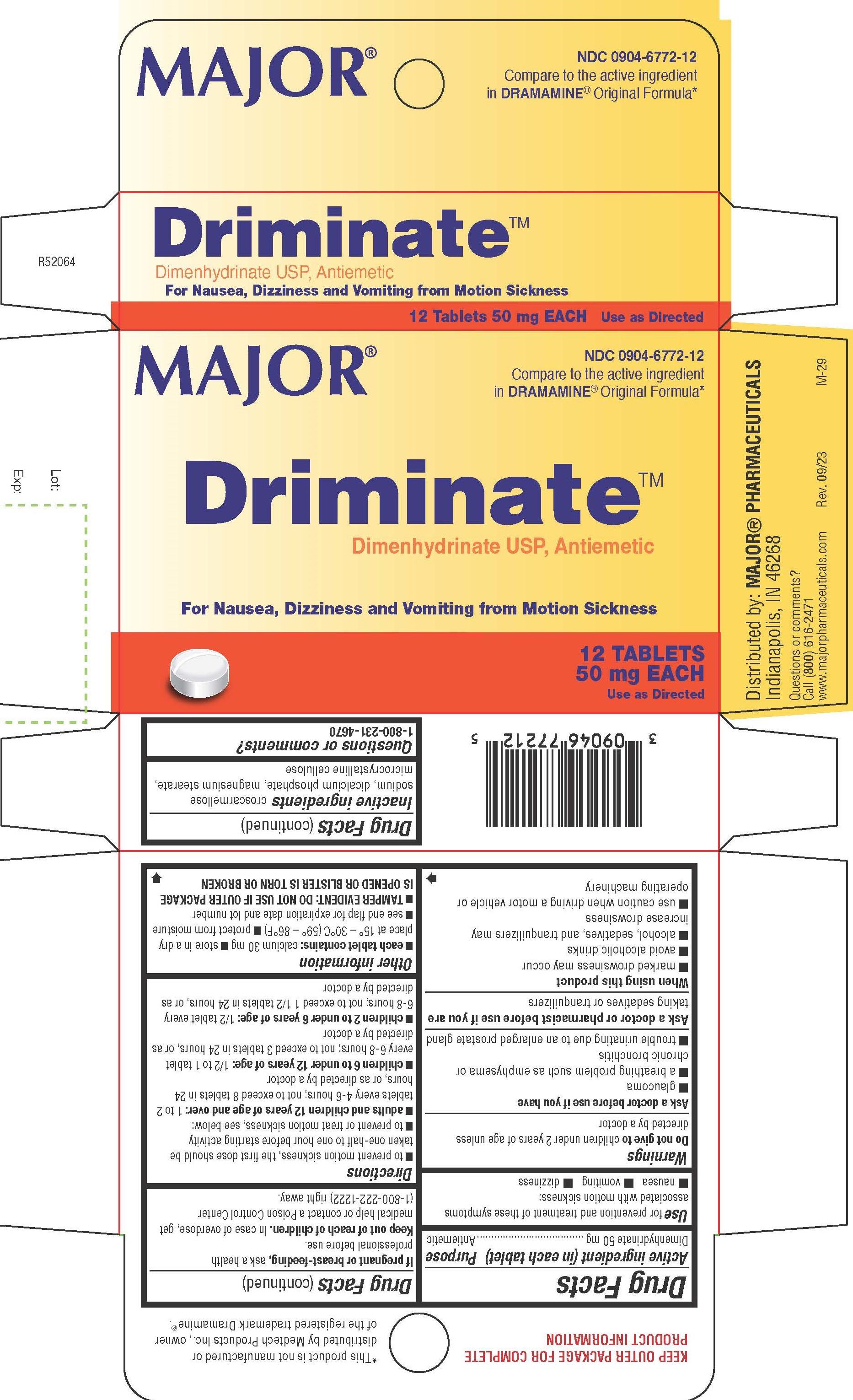 DRUG LABEL: Dimenhydrinate
NDC: 0904-6772 | Form: TABLET
Manufacturer: Major Pharmaceuticals
Category: otc | Type: HUMAN OTC DRUG LABEL
Date: 20250813

ACTIVE INGREDIENTS: DIMENHYDRINATE 50 mg/1 1
INACTIVE INGREDIENTS: CROSCARMELLOSE SODIUM; DIBASIC CALCIUM PHOSPHATE DIHYDRATE; MAGNESIUM STEARATE; MICROCRYSTALLINE CELLULOSE

1006-Major

Drug Facts

Active ingredient (in each tablet)

Dimenhydrinate 50 mg

Purpose

Antiemetic

Uses

for the prevention and treatment of nausea, vomiting, or dizziness associated with motion sickness

WARNINGS

Do not give to children under 2 years of age unless directed by a doctor

Ask a doctor before use if you have

■ glaucoma

■ a breathing problem such as emphysema or chronic bronchitis

■ trouble urinating due to an enlarged prostate gland

Ask a doctor or pharmacist before use if you are taking sedatives or tranquilizers

When using this product

■ marked drowsiness may occur

■ avoid alcoholic drinks

■ alcohol, sedatives, and tranquilizers may increase drowsiness

■ use caution when driving a motor vehicle or operating machinery

PREGNANCY OR BREAST FEEDING

If pregnant or breast-feeding, ask a health professional before use.

.

Keep out of reach of children.

OVERDOSAGE

In case of overdose, get medical help or contact a Poison Control Center (1-800-222-1222) right away.

Directions

■ to prevent motion sickness, the rst dose should be taken one-half to one hour before starting activity

■ adults and children 12 years of age and over: 1 to 2 tablets every 4-6 hours; not to exceed 8 tablets in 24 hours, or as directed by a doctor

■ children 6 to under 12 years of age: 1/2 to 1 tablet every 6-8 hours; not to exceed 3 tablets in 24 hours, or as directed by a doctor

■ children 2 to under 6 years of age: 1/2 tablet every 6-8 hours; not to exceed 1 1/2 tablets in 24 hours, or as directed by a doctor

Other information

■ each tablet contains: calcium 30 mg

■ store in a dry place at 15° – 30°C (59° – 86°F)

■ protect from moisture

■ see end -ap for expiration date and lot number

■ TAMPER EVIDENT: DO NOT USE IF OUTER PACKAGE IS OPENED OR BLISTER IS TORN OR BROKEN

INACTIVE INGREDIENT

croscarmellose sodium, dicalcium phosphate, magnesium stearate, microcrystalline cellulose

Questions or comments?

1-800-231-4670

KEEP OUTER PACKAGE FOR COMPLETE PRODUCT INFORMATION

*This product is not manufactured or distributed by Medtech Products Inc., owner of the registered trademark Dramamine®.

Distributed by: MAJOR® PHARMACEUTICALS
Indianapolis, IN 46268
Questions or comments?
Call (800) 616-2471
www.majorpharmaceuticals.com

PACKAGE LABEL

MAJOR®

NDC 0904-6772-12

Compare to the Active Ingredient in DRAMAMINE® Original Formula*

DriminateTM

Dimenhydrinate USP, Antiemetic

For Nausea, Dizziness and Vomiting from Motion Sickness

12 Tablets 50mg Each

Use as Directed